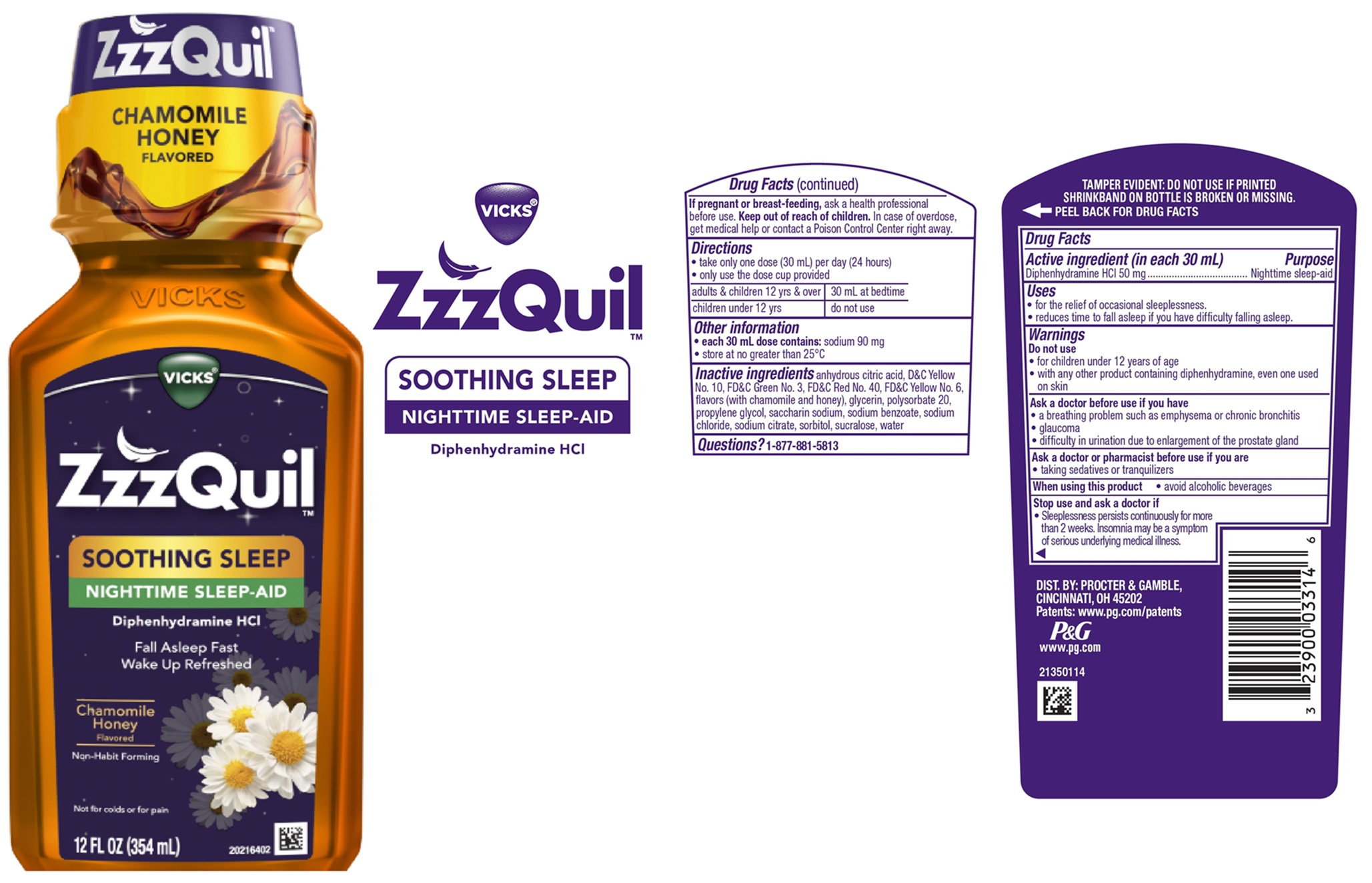 DRUG LABEL: Vicks ZzzQuil
NDC: 69423-830 | Form: LIQUID
Manufacturer: The Procter & Gamble Manufacturing Company
Category: otc | Type: HUMAN OTC DRUG LABEL
Date: 20251202

ACTIVE INGREDIENTS: DIPHENHYDRAMINE HYDROCHLORIDE 50 mg/30 mL
INACTIVE INGREDIENTS: TRISODIUM CITRATE DIHYDRATE; ANHYDROUS CITRIC ACID; FD&C GREEN NO. 3; FD&C YELLOW NO. 6; CHAMOMILE; D&C YELLOW NO. 10; HONEY; PROPYLENE GLYCOL; SODIUM CHLORIDE; GLYCERIN; POLYSORBATE 20; SORBITOL; SUCRALOSE; FD&C RED NO. 40; WATER; SACCHARIN SODIUM; SODIUM BENZOATE

Vicks ZzzQuil™ SOOTHING SLEEP NIGHTTIME SLEEP-AID

Drug Facts

Active ingredient (in each 30 mL)

Diphenhydramine HCl 50 mg

Purpose

Nighttime sleep-aid

Uses

- for the relief of occasional sleeplessness
- reduces time to fall asleep if you have difficulty falling asleep

Warnings

Do not use

- for children under 12 years of age
- with any other product containing diphenhydramine, even one used on skin

Ask a doctor before use if you have

- a breathing problem such as emphysema or chronic bronchitis
- glaucoma
- difficulty in urination due to enlargement of the prostate gland
- a sodium-restricted diet

Ask a doctor or pharmacist before use if you are

- taking sedatives or tranquilizers

When using this product

- avoid alcoholic beverages

Stop use and ask a doctor if

- sleeplessness persists continuously for more than 2 weeks. Insomnia may be a symptom of serious underlying medical illness.

If pregnant or breast-feeding,

ask a health professional before use.

Keep out of reach of children.

OVERDOSAGE

In case of overdose, get medical help or contact a Poison Control Center right away.

Directions

• take only one dose (30 mL) per day (24 hours)
• only use the dose cup provided

adults & children 12 yrs & over | 30 mL at bedtime
children under 12 yrs | do not use

Other information

- each 30 mL dose contains: sodium 152 mg
- store at no greater than 25°C

Inactive ingredients

anhydrous citric acid, D&C Yellow No. 10, FD&C Green No. 3, FD&C Red No. 40, FD&C Yellow No. 6, flavors (with chamomile and honey), glycerin, polysorbate 20, propylene glycol, saccharin sodium, sodium benzoate, sodium chloride, sodium citrate, sorbitol, sucralose, water

Questions?

1-877-881-5813

TAMPER EVIDENT: DO NOT USE IF PRINTED SHRINKBAND ON BOTTLE IS BROKEN OR MISSING.

DIST. BY PROCTER & GAMBLE,

CINCINNATI, OH 45202

PRINCIPAL DISPLAY PANEL - 354 ml Bottle Label

VICKS®

ZzzQuil™

SOOTHING SLEEP

NIGHTTIME SLEEP-AID

Diphenhydramine HCl

Fall Asleep Fast

Wake Up Refreshed

Chamomile Honey Flavored

Non-Habit Forming

Not for colds or for pain

12 FL OZ (354 ml)